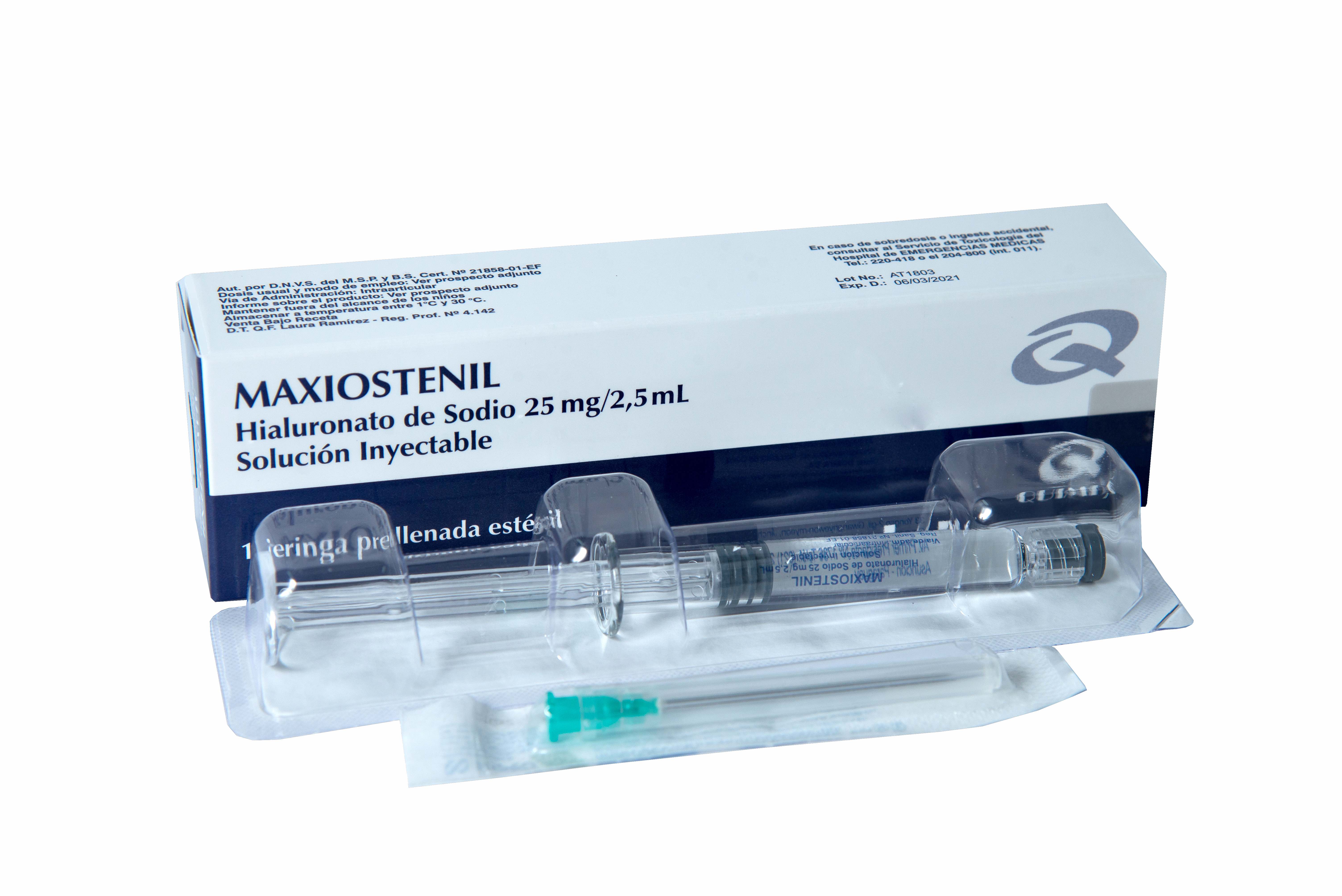 DRUG LABEL: Hyaluronic Acid
NDC: 77651-4162 | Form: INJECTION
Manufacturer: Quimfa S.A
Category: prescription | Type: HUMAN PRESCRIPTION DRUG LABEL
Date: 20200605

ACTIVE INGREDIENTS: HYALURONIC ACID 2.5 g/1 1

Precautions and Warnings

* Si se observase derrame articular extraerlo antes de inyectar Maxiostenil.
* Es necesario seguir la técnica correcta de la inyección intraarticular en condiciones completamente asépticas.
Ver Instrucciones de uso y manipulación.
* Como en cualquier procedimiento intraarticular, es recomendable evitar la sobrecarga de la articulación
tratada, inmediatamente después de la inyección intraarticular.
* Los pacientes deben ser cuidadosamente examinados antes de la administración de Maxiostenil para
determinar posibles signos de inflamación agudos y el médico debe evaluar cuidadosamente la oportunidad del
inicio de la terapia.
* Se debe observar particular atención en pacientes con infecciones o alteraciones de la piel en zonas próximas
al punto de inyección para evitar la posibilidad de desarrollar artritis bacteriana.

* Guardar fuera del alcance de los niños.